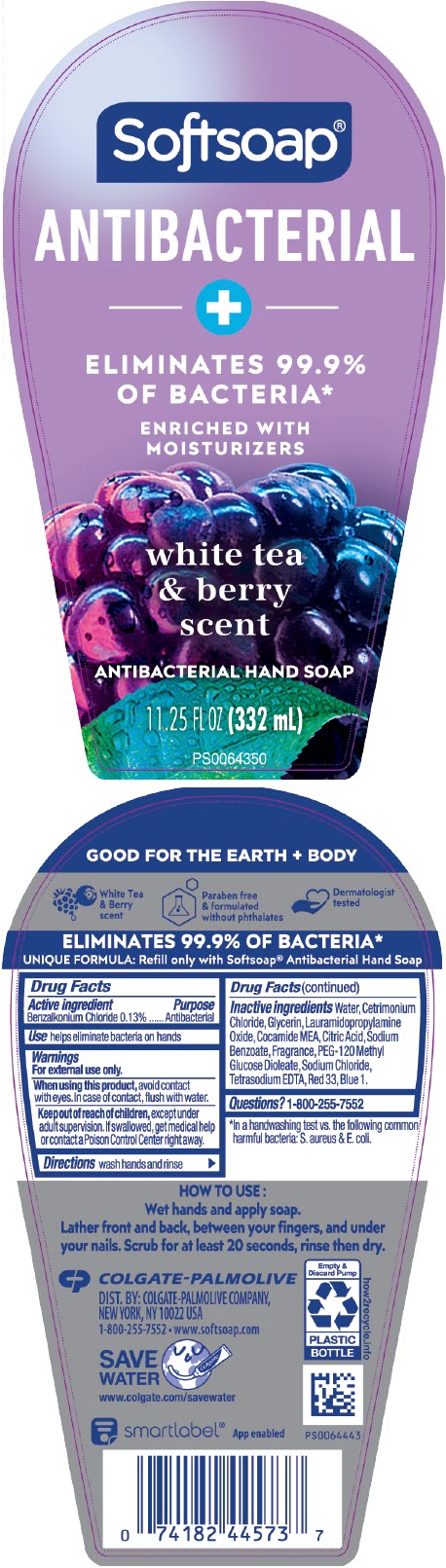 DRUG LABEL: Softsoap Antibacterial with Moisturizers White Tea and Berry
NDC: 35000-243 | Form: LIQUID
Manufacturer: COLGATE PALMOLIVE COMPANY
Category: otc | Type: HUMAN OTC DRUG LABEL
Date: 20241121

ACTIVE INGREDIENTS: BENZALKONIUM CHLORIDE 1.33 mg/1 mL
INACTIVE INGREDIENTS: WATER; CETRIMONIUM CHLORIDE; GLYCERIN; LAURAMIDOPROPYLAMINE OXIDE; COCO MONOETHANOLAMIDE; ANHYDROUS CITRIC ACID; SODIUM BENZOATE; PEG-120 METHYL GLUCOSE DIOLEATE; SODIUM CHLORIDE; EDETATE SODIUM; D&C RED NO. 33; FD&C BLUE NO. 1

Softsoap® Antibacterial with Moisturizers White Tea and Berry

Drug Facts

Active ingredient

Benzalkonium Chloride 0.13%

Purpose

Antibacterial

Use

helps eliminate bacteria on hands

Warnings

For external use only.

When using this product, avoid contact with eyes. In case of contact, flush with water.

Keep out of reach of children, except under adult supervision. If swallowed, get medical help or contact a Poison Control Center right away.

Directions

wash hands and rinse

Inactive ingredients

Water, Cetrimonium Chloride, Glycerin, Lauramidopropylamine Oxide, Cocamide MEA, Citric Acid, Sodium Benzoate, Fragrance, PEG-120 Methyl Glucose Dioleate, Sodium Chloride, Tetrasodium EDTA, Red 33, Blue 1.

Questions?

1-800-255-7552

DIST. BY: COLGATE-PALMOLIVE COMPANY,
NEW YORK, NY 10022 USA

PRINCIPAL DISPLAY PANEL - 332 mL Bottle Label

Softsoap®

ANTIBACTERIAL

+

ELIMINATES 99.9%
OF BACTERIA*

ENRICHED WITH
MOISTURIZERS

white tea
& berry
scent

ANTIBACTERIAL HAND SOAP

11.25 FL OZ (332 mL)

PS0064350